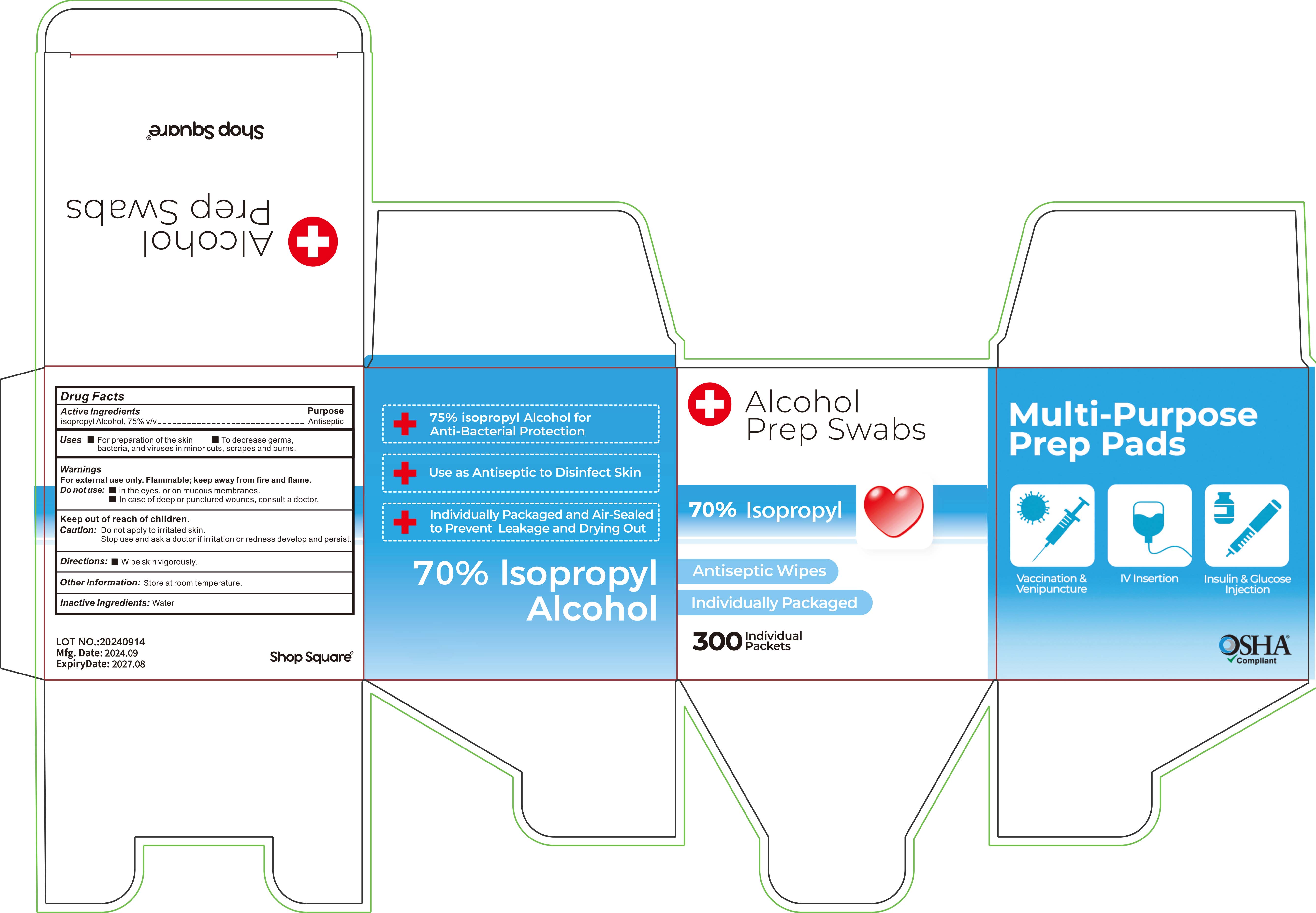 DRUG LABEL: Alcohol Prep Awabs
NDC: 84899-001 | Form: PATCH
Manufacturer: Enlightening Pallet Industry Co., Limited
Category: otc | Type: HUMAN OTC DRUG LABEL
Date: 20260114

ACTIVE INGREDIENTS: ISOPROPYL ALCOHOL 70 mL/100 mL
INACTIVE INGREDIENTS: WATER

84899-001

Active Ingredients

Isopropyl Alcohol, 70% v/v

Purose

Antiseptic

Uses

■For preparation of the skin

■To decrease germs, bacteria, and viruses in minor cuts, scrapes and burns.

Warnings

For external use only. Flammable; keep away from fire and flame.

Do not use:

■ In the eyes, or on mucous membranes.
■ In case of deep or punctured wounds, consult a doctor.

Caution:

Do not apply to iritated skin.

Stop use and ask a doctor if iritation or redness develop and persist.

Directions:

■ Wipe skin vigorously.

Other Information

Store at room temperature.

Inactive Ingredients:

Water